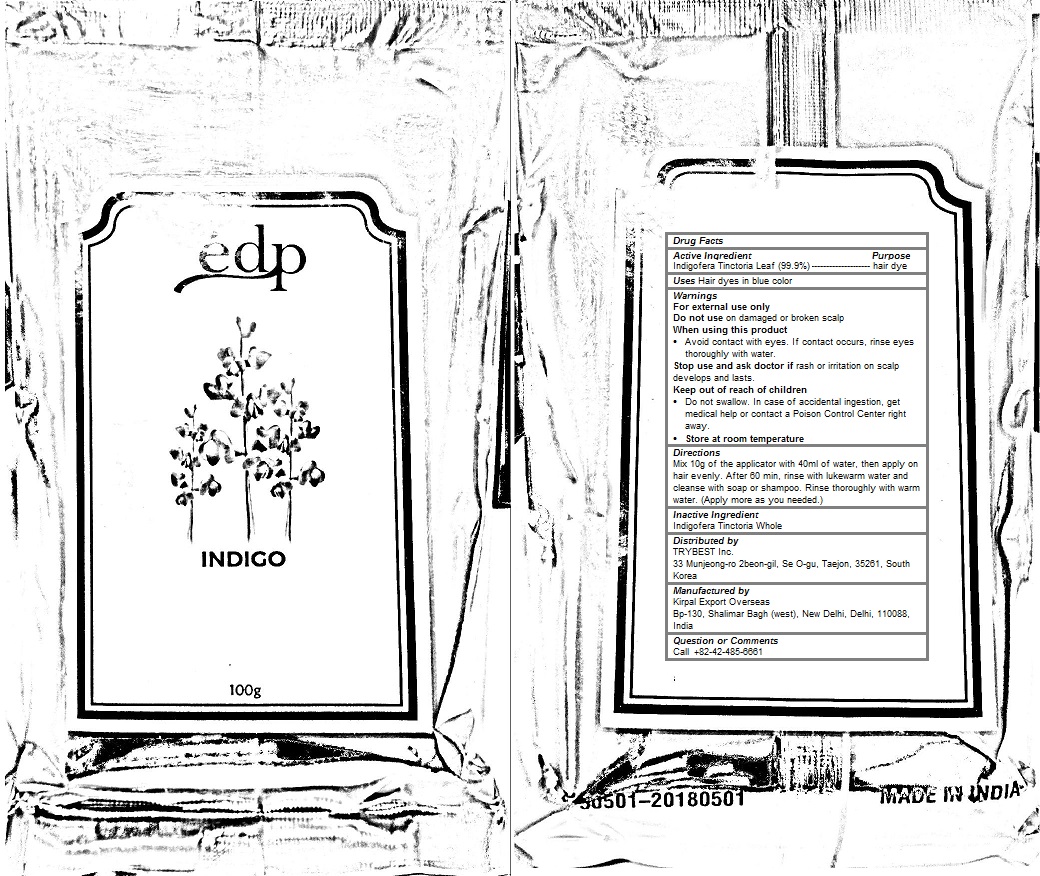 DRUG LABEL: EDP INDIGO
NDC: 70434-102 | Form: POWDER
Manufacturer: EDP Inc.
Category: otc | Type: HUMAN OTC DRUG LABEL
Date: 20190115

ACTIVE INGREDIENTS: INDIGOFERA TINCTORIA LEAF 0.999 1/100 g
INACTIVE INGREDIENTS: INDIGOFERA TINCTORIA WHOLE 0.001 1/100 g

EDP INDIGO